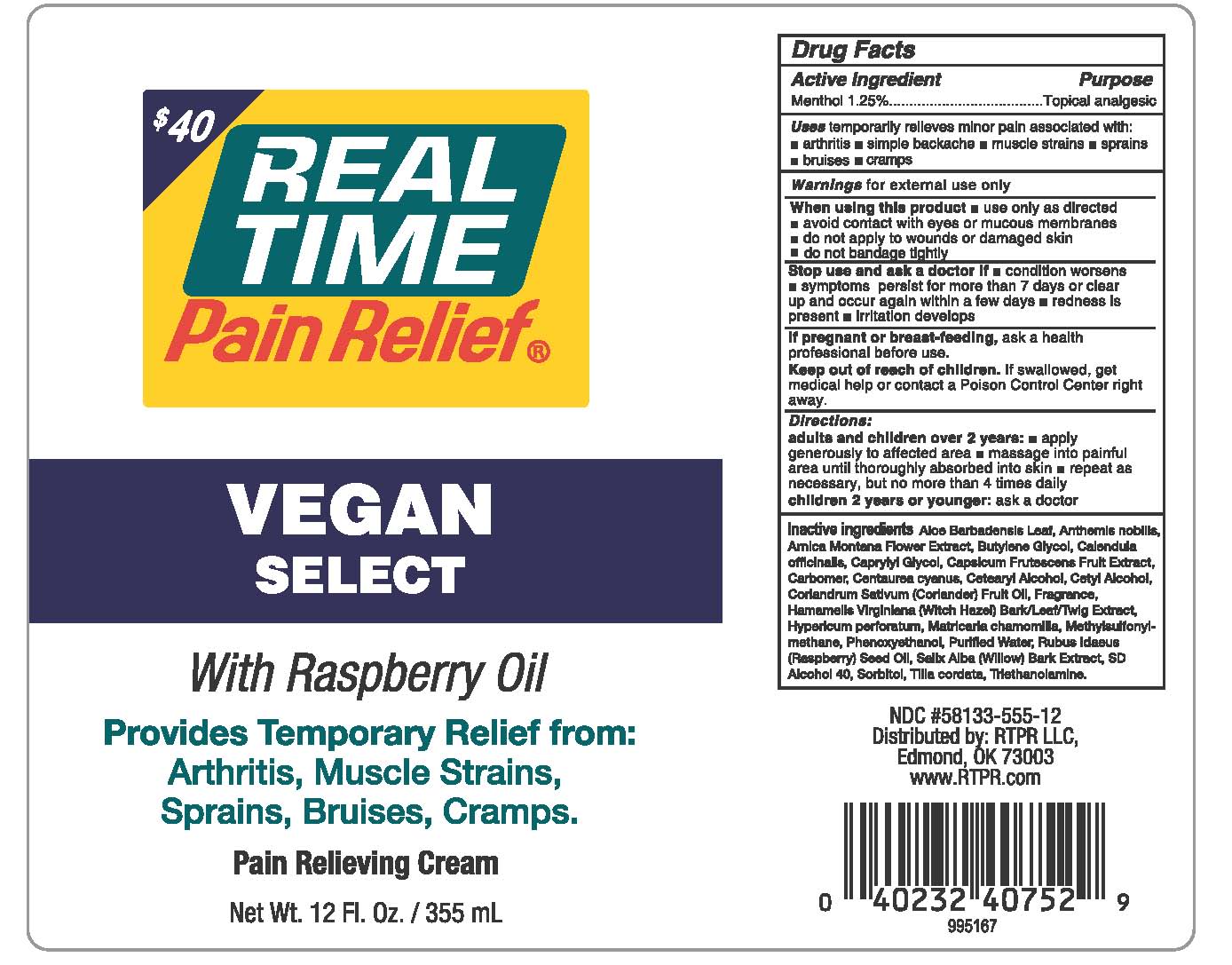 DRUG LABEL: Real Time Pain Relief Vegan Select
NDC: 58133-555 | Form: LOTION
Manufacturer: Cosmetic Specialty Labs, Inc.
Category: otc | Type: HUMAN OTC DRUG LABEL
Date: 20180117

ACTIVE INGREDIENTS: MENTHOL 1.25 g/100 mL
INACTIVE INGREDIENTS: ALOE VERA LEAF; ARNICA MONTANA FLOWER; CAPSICUM FRUTESCENS WHOLE; ANTHEMIS ARVENSIS FLOWERING TOP; BUTYLENE GLYCOL; CARBOMER 940; CORIANDRUM SATIVUM WHOLE; WATER; CALENDULA OFFICINALIS SEED OIL; CENTAUREA CYANUS FLOWER; HYPERICUM PERFORATUM; PHENOXYETHANOL; CETOSTEARYL ALCOHOL; HAMAMELIS VIRGINIANA BARK; SALIX ALBA BARK; TERT-BUTYL ALCOHOL; MATRICARIA CHAMOMILLA FLOWERING TOP OIL; 3,4-METHYLENEDIOXYBENZYL METHYLSULFONE; CETYL ALCOHOL; CAPRYLYL GLYCOL; SORBITOL; TILIA CORDATA FLOWER; TRIETHANOLAMINE TRIS(DIHYDROGEN PHOSPHATE); RUBUS IDAEUS FRUIT VOLATILE OIL

Real Time Pain Relief Cream Vegan Select

Active Ingredient

Menthol 1.25%

Purpose

Topical Analgesic

Uses

temporarily relieves minor pain associated with:

- arthritis
- simple backache
- muscle strains
- sprains
- bruises
- cramps

Warnings

for external use only

When using this product

- avoid contact with eyes or mucous membranes
- do not apply to wounds or damaged skin
- do not bandage tightly

Stop use and ask a doctor if

- condition worsens
- symptoms persist for more than 7 days or clear up and occur again within a few days
- redness is present
- irritation develops

If pregnant or breast-feeding,

ask a health professional before use

Keep out of reach of children

If swallowed, get medical help or contact a Poison Control Center right away.

Directions:

adults and children over 2 years:

- apply generously to affected area
- massage into painful area until thoroughly absorbed into skin
- repeat as necessary, but no more than 4 times daily

children 2 years or younger: ask a doctor

Inactive ingredients:

Aloe Barbadensis Leaf, Anthemis nobilis, Arnica Montana Flower Extract, Butylene Glycol , Calendula officinalis, Caprylyl Glycol, Capsicum Frutescens Fruit Extract, Carbomer, Centaurea cyanus, Cetearyl Alcohol, Cetyl Alcohol, Coriandrum Sativum (Coriander) Fruit Oil, Fragrance, Hamamelis Virginiana (Witch Hazel) Bark/Leaf/Twig Extract, Hypericum perforatum, Matricaria chamomilla, Methylsulfonylmethane, Phenoxyethanol, Purified Water, Rubus Idaeus (Raspberry) Seed Oil, Salix Alba (Willow) Bark Extract, SD Alcohol 40, Sorbitol, Tilia cordata, Triethanolamine.